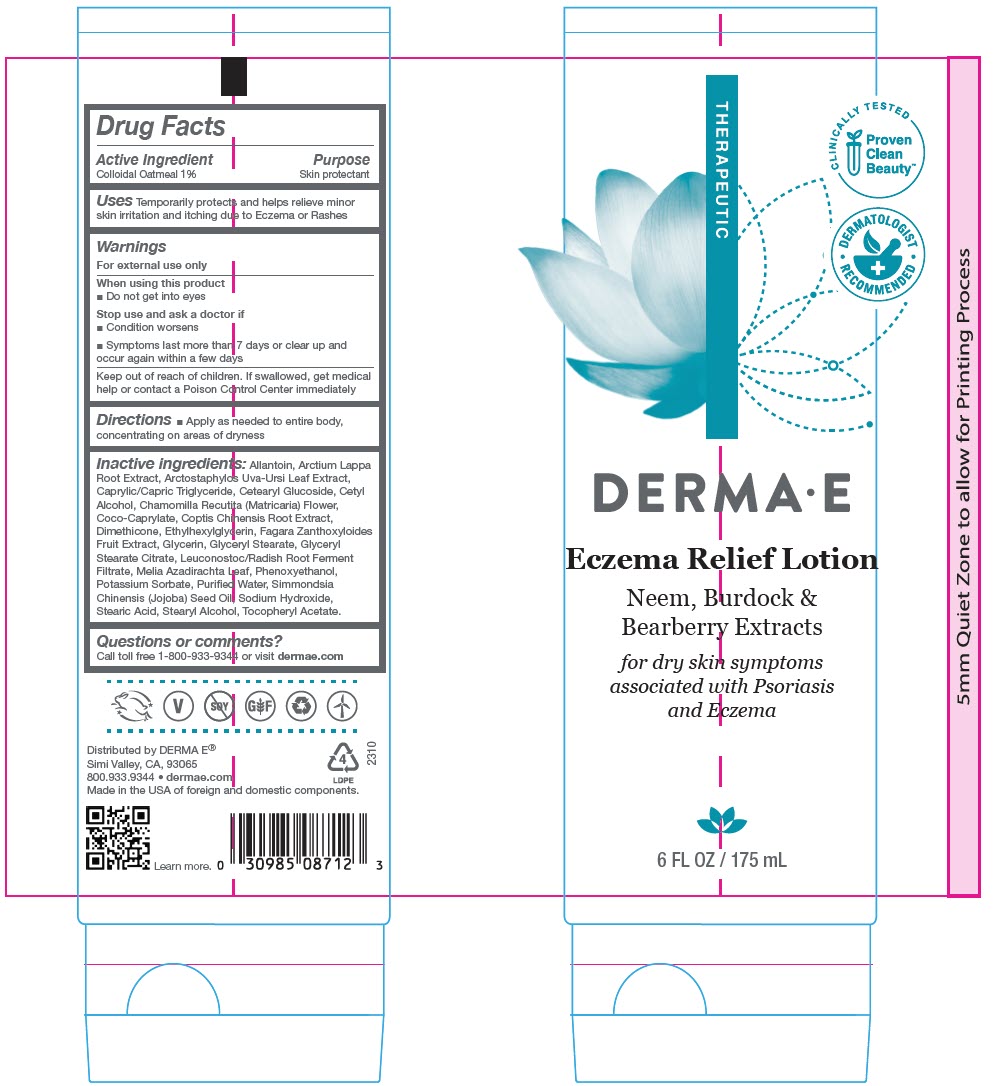 DRUG LABEL: Derma E Eczema Relief
NDC: 54108-8712 | Form: LOTION
Manufacturer: derma e
Category: otc | Type: HUMAN OTC DRUG LABEL
Date: 20240618

ACTIVE INGREDIENTS: OATMEAL 10 mg/1 mL
INACTIVE INGREDIENTS: ALLANTOIN; ARCTIUM LAPPA ROOT; ARCTOSTAPHYLOS UVA-URSI LEAF; MEDIUM-CHAIN TRIGLYCERIDES; CETOSTEARYL ALCOHOL; CETEARYL GLUCOSIDE; CETYL ALCOHOL; MATRICARIA CHAMOMILLA FLOWERING TOP; COCO-CAPRYLATE; COPTIS CHINENSIS ROOT; DIMETHICONE; ETHYLHEXYLGLYCERIN; GLYCERIN; GLYCERYL STEARATE SE; GLYCERYL STEARATE CITRATE; LEUCONOSTOC/RADISH ROOT FERMENT FILTRATE; AZADIRACHTA INDICA LEAF; PHENOXYETHANOL; POTASSIUM SORBATE; WATER; JOJOBA OIL; SODIUM HYDROXIDE; STEARIC ACID D7; STEARYL ALCOHOL; .ALPHA.-TOCOPHEROL ACETATE, DL-

Derma E Eczema Relief

Drug Facts

Active Ingredient

Colloidal Oatmeal 1%

Purpose

Skin protectant

Uses

Temporarily protects and helps relieve minor skin irritation and itching due to Eczema or Rashes

Warnings

For external use only

When using this product

- Do not get into eyes

Stop use and ask a doctor if

- Condition worsens
- Symptoms last more than 7 days or clear up and occur again within a few days

Keep out of reach of children. If swallowed, get medical help or contact a Poison Control Center immediately

Directions

- Apply as needed to entire body, concentrating on areas of dryness

Inactive ingredients

Allantoin, Arctium Lappa Root Extract, Arctostaphylos Uva-Ursi Leaf Extract, Caprylic/Capric Triglyceride, Cetearyl Glucoside, Cetyl Alcohol, Chamomilla Recutita (Matricaria) Flower, Coco-Caprylate, Coptis Chinensis Root Extract, Dimethicone, Ethylhexylglycerin, Fagara Zanthoxyloides Fruit Extract, Glycerin, Glyceryl Stearate, Glyceryl Stearate Citrate, Leuconostoc/Radish Root Ferment Filtrate, Melia Azadirachta Leaf, Phenoxyethanol, Potassium Sorbate, Purified Water, Simmondsia Chinensis (Jojoba) Seed Oil, Sodium Hydroxide, Stearic Acid, Stearyl Alcohol, Tocopheryl Acetate.

Questions or comments?

Call toll free 1-800-933-9344 or visit dermae.com

Distributed by DERMA E®
Simi Valley, CA, 93065

PRINCIPAL DISPLAY PANEL - 175 mL Tube Label

THERAPEUTIC

CLINICALLY TESTED

Proven
Clean
Beauty™

DERMATOLOGIST
• RECOMMENDED •

DERMA • E

Eczema Relief Lotion

Neem, Burdock &
Bearberry Extracts

for dry skin symptoms
associated with Psoriasis
and Eczema

6 FL OZ / 175 mL